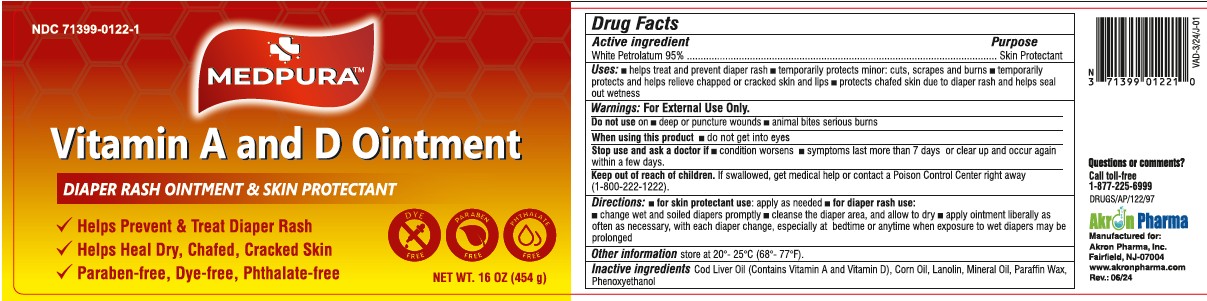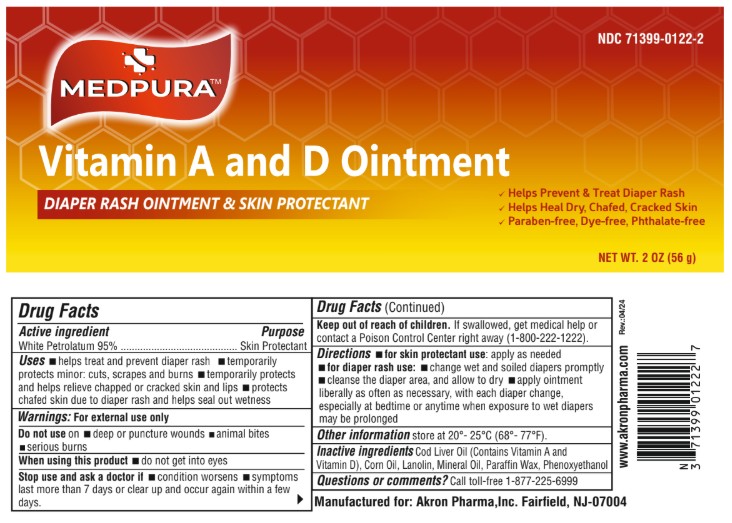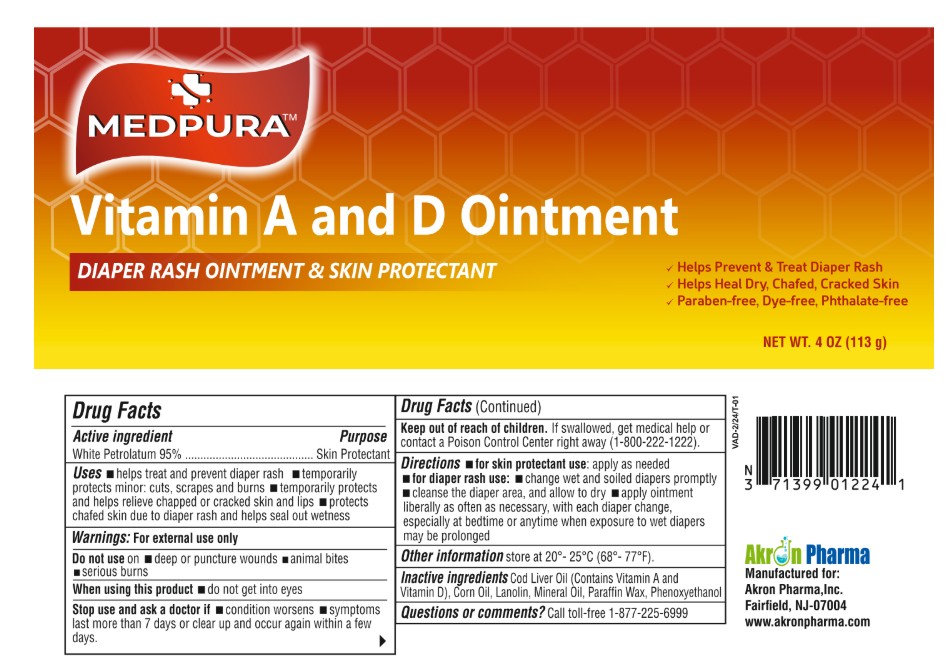 DRUG LABEL: MEDPURA Vitamin A and D

NDC: 71399-0122 | Form: OINTMENT
Manufacturer: Akron Pharma Inc.
Category: otc | Type: HUMAN OTC DRUG LABEL
Date: 20260114

ACTIVE INGREDIENTS: PETROLATUM 95 g/100 g
INACTIVE INGREDIENTS: COD LIVER OIL; LANOLIN; MINERAL OIL; PARAFFIN; PHENOXYETHANOL

MEDPURA
VITAMIN A and D Ointment

Active Ingredient

White Petrolatum USP (95%)

Purpose

Skin Protectant

Uses

■ helps treat and prevent diaper rash ■ helps seal out wetness ■ temporarily protects minor ■ cuts ■ scrapes ■ burns ■ temporarily helps protect and relieve chapped and cracked skin or lips ■ helps prevent and protect from the drying effects of wind and cold weather ■ helps prevent and protect chafed skin or minor skin irritations associated with diaper rash ■ with each diaper change, espicially at bedtime when exposure to wet diapers may be prolonged

Warnings

For external use only

When using this product

■ do not get into eyes

Stop use and ask a doctor if

■ condition worsens ■ symptoms last more than 7 days or clear up and occur again in a few days

Do not use on

■ animal bites ■ deep or puncture wounds ■ serious burns

Keep out of reach of children.If swallowed, get medical help or contact a Poison Control Center right away

Directions

■ helps seal out wetness ■ temporarily protects minor ■ cuts ■ scrapes ■ burns ■ temporarily helps protect and relieve chapped and cracked skin or lips ■ helps prevent and protect from the drying effects of wind and cold weather ■ helps prevent and protect chafed skin or minor skin irritations associated with diaper rash ■ with each diaper change, espicially at bedtime when exposure to wet diapers may be prolonged

Other Information

store at 20°- 25°C (68°- 77°F).

Inactive ingredients

cod liver oil (vitamin A and D), lanolin, mineral oil, paraffin wax, phenoxyethanol

Questions or comments?

Call toll-free 1-877-225-6999

Manufactured for:

Akron Pharma,Inc.

Fairfield, NJ 07004